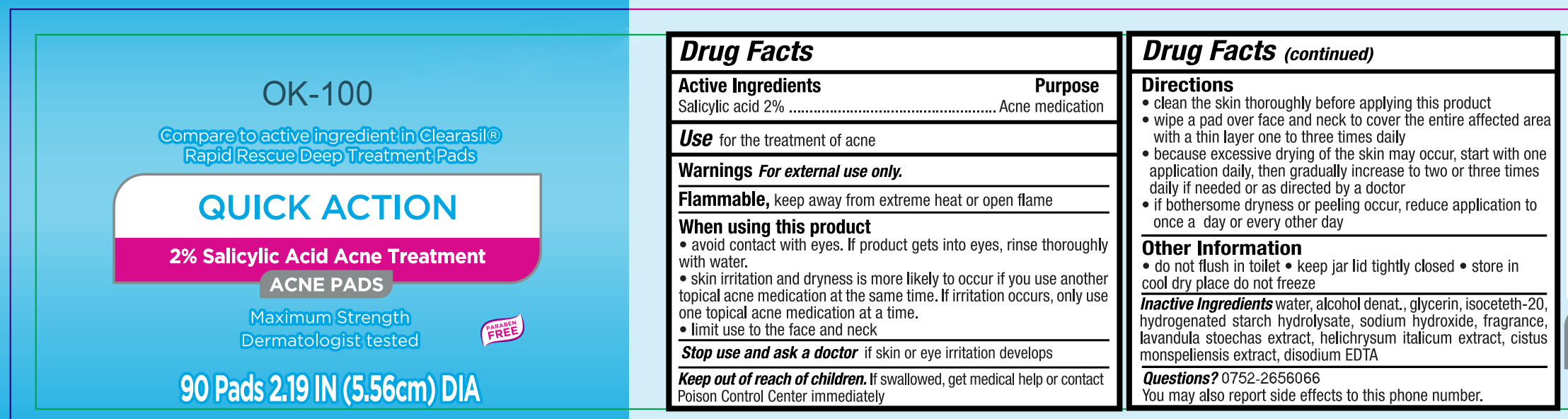 DRUG LABEL: Salicylic acid cotton sheet
NDC: 81950-001 | Form: TABLET
Manufacturer: Pang's International Holdings Limited
Category: otc | Type: HUMAN OTC DRUG LABEL
Date: 20210525

ACTIVE INGREDIENTS: SALICYLIC ACID 2 g/100 1
INACTIVE INGREDIENTS: ALCOHOL; HYDROGENATED STARCH HYDROLYSATE; SODIUM HYDROXIDE; FRAGRANCE CLEAN ORC0600327; CISTUS MONSPELIENSIS LEAF; EDETATE DISODIUM ANHYDROUS; LAVANDULA STOECHAS WHOLE; HELICHRYSUM ITALICUM FLOWER; GLYCERIN; ISOCETETH-20; WATER

81950-001
Salicylic acid cotton sheet

Active Ingredient(s)

Salicylic acid 2%...........Acne medication

Purpose

Acne medication

Use

Use for the treatment of acne.

Warnings

Warnings For external use only.
Flammable, keep away from extreme heat or open flame.

Do not use

/

WHEN USING

avoid contact with eyes.If product gets into eyes, rinse thoroughly with water.
skin irritation and dryness is more likely to occur if you use another topical acne medication at the sametime.lf irritation occurs, onlyy use one topical acne medication at a time.
limit use to the face and neck.

Stop use and ask a doctor if skin or eye irritation develops.

Keep out of reach of children.If swallowed, get medical help or contact Poison Control Center immediately.

Stop use and ask a doctor if skin or eye irritation develops.

Keep out of reach of children.If swallowed, get medical help or contact Poison Control Center immediately.

Directions

clean the skin thoroughly before applying this product.
wipe a pad over face and neck to cover the entire affected area with a thin layer one to three times daily.
because excessive drying of the skin may occur, start with one application daily, then gradually increase to two or three times daily if needed or as directed by a doctor.
if bothersome dryness or peeling occur, reduce application to once a day or every other day.

Other information

do not flush in toilet.
keep jar lid tightly closed.
store in cool dry place do not freeze.

Inactive ingredients

water, alcohol den at., glycerin, isoceteth-20, hydrogenated starch hydrolysate, sodium hydroxide, fragrance, lavandula stoechas extract, helichrysum italicum extract, cistus monspeliensis extract, disodium EDTA

Questions

86-0752-2656066
You may also report side effects to this phone number.

Package Label - Principal Display Panel

81950-001-01 90 PADS